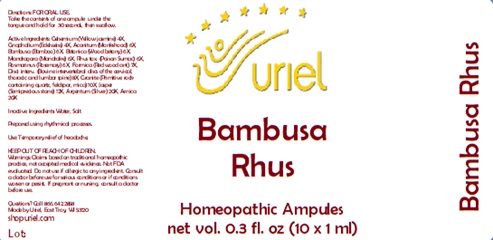 DRUG LABEL: Bambusa Rhus
NDC: 48951-2016 | Form: LIQUID
Manufacturer: Uriel Pharmacy Inc.
Category: homeopathic | Type: HUMAN OTC DRUG LABEL
Date: 20241213

ACTIVE INGREDIENTS: GELSEMIUM SEMPERVIRENS ROOT 4 [hp_X]/1 mL; PSEUDOGNAPHALIUM LUTEOALBUM LEAF 4 [hp_X]/1 mL; ACONITUM NAPELLUS 6 [hp_X]/1 mL; BAMBUSA VULGARIS WHOLE 6 [hp_X]/1 mL; STACHYS OFFICINALIS 6 [hp_X]/1 mL; MANDRAGORA OFFICINARUM ROOT 6 [hp_X]/1 mL; TOXICODENDRON PUBESCENS LEAF 6 [hp_X]/1 mL; ROSMARINUS OFFICINALIS FLOWERING TOP 6 [hp_X]/1 mL; FORMICA RUFA 7 [hp_X]/1 mL; BOS TAURUS INTERVERTEBRAL DISC 8 [hp_X]/1 mL; PENOXSULAM 10 [hp_X]/1 mL; SILICON DIOXIDE 12 [hp_X]/1 mL; SILVER 20 [hp_X]/1 mL; ARNICA MONTANA 20 [hp_X]/1 mL
INACTIVE INGREDIENTS: WATER; SODIUM CHLORIDE

Bambusa Rhus

INDICATIONS AND USAGE

Directions: FOR ORAL USE.

DOSAGE AND ADMINISTRATION

Take the contents of one ampule
under the tongue and hold for
30 seconds, then swallow.

Active Ingredients: Gelsemium (Yellow jasmine) 4X,
Gnaphalium (Edelweiss) 4X, Aconitum (Monkshood) 6X, Bambusa (Bamboo) 6X, Betonica (Wood betony) 6X, Mandragora (Mandrake) 6X, Rhus tox. (Poison Sumac) 6X, Rosmarinus (Rosemary) 6X, Formica (Red wood ant) 7X, Disci interv. (Bovine intervertebral discs of the cervical, thoracic and lumbar spine) 8X, Granite (Primitive rock containing quartz, feldspar, mica) 10X, Jasper (Semiprecious stone) 12X, Argentum (Silver) 20X, Arnica 20X

Inactive Ingredients: Water, Salt

Prepared using rhythmical processes.

PURPOSE

Use: Temporary relief of headache.

KEEP OUT OF REACH OF CHILDREN.

WARNINGS

Warnings: Claims based on traditional homeopathic practice, not accepted medical evidence. Not FDA evaluated. Do not use if allergic to any ingredient. Consult a doctor before use for serious conditions or if conditions worsen or persist. If pregnant or nursing, consult a doctor before use.

Questions? Call 866.642.2858
Uriel, East Troy, WI 53120
shopuriel.com Lot: